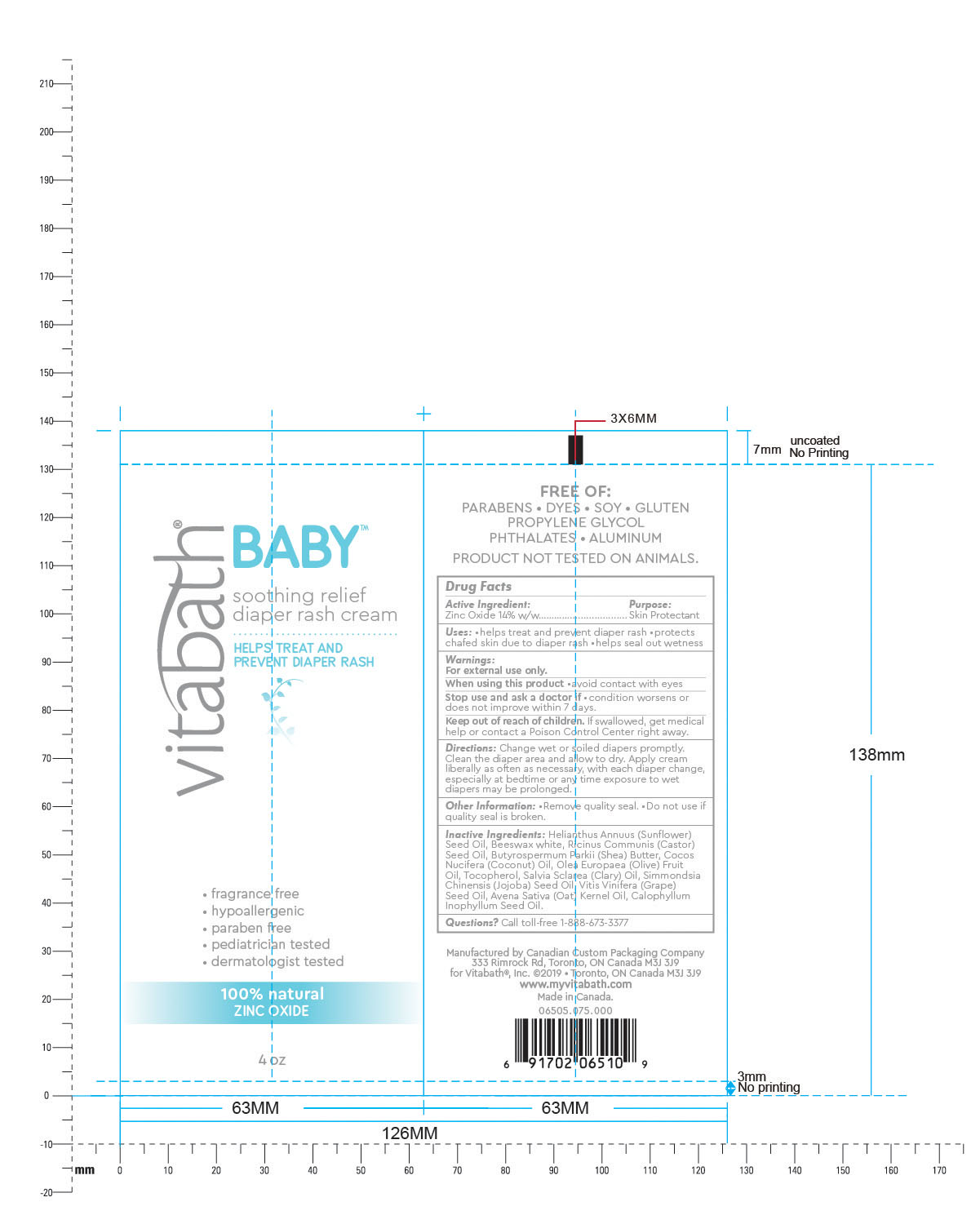 DRUG LABEL: Vitabath Baby Soothing Relief Diaper Rash
NDC: 73172-004 | Form: CREAM
Manufacturer: Vitabath Inc.
Category: otc | Type: HUMAN OTC DRUG LABEL
Date: 20190613

ACTIVE INGREDIENTS: ZINC OXIDE 14 g/100 g
INACTIVE INGREDIENTS: TAMANU OIL; GRAPE SEED OIL; SUNFLOWER OIL; WHITE WAX; CASTOR OIL; SHEA BUTTER; OAT KERNEL OIL; COCONUT OIL; OLIVE OIL; TOCOPHEROL; CLARY SAGE OIL; JOJOBA OIL

Vitabath Baby Soothing Relief Diaper Rash Cream

Active Ingredients

Zinc Oxide 14% w/w

Purpose

Skin protectant

Uses

Uses: •helps treat and prevent diaper rash •protects
chafed skin due to diaper rash •helps seal out wetness

Warnings

For external use only.

When using this product •avoid contact with eyes

When using this product •avoid contact with eyes

Stop use and ask a doctor if •condition worsens or
does not improve within 7 days.

Keep out of reach of children. If swallowed, get medical
help or contact a Poison Control Center right away.

DOSAGE AND ADMINISTRATION

Directions: Change wet or soiled diapers promptly.
Clean the diaper area and allow to dry. Apply cream
liberally as often as necessary, with each diaper change,
especially at bedtime or any time exposure to wet
diapers may be prolonged.

Other Information: •Remove quality seal. •Do not use if
quality seal is broken.

Inactive Ingredients: Helianthus Annuus (Sunflower)
Seed Oil, Beeswax white, Ricinus Communis (Castor)
Seed Oil, Butyrospermum Parkii (Shea) Butter, Cocos
Nucifera (Coconut) Oil, Olea Europaea (Olive) Fruit
Oil, Tocopherol, Salvia Sclarea (Clary) Oil, Simmondsia
Chinensis (Jojoba) Seed Oil, Vitis Vinifera (Grape)
Seed Oil, Avena Sativa (Oat) Kernel Oil, Calophyllum
Inophyllum Seed Oil.

Questions? Call toll-free 1-888-673-3377